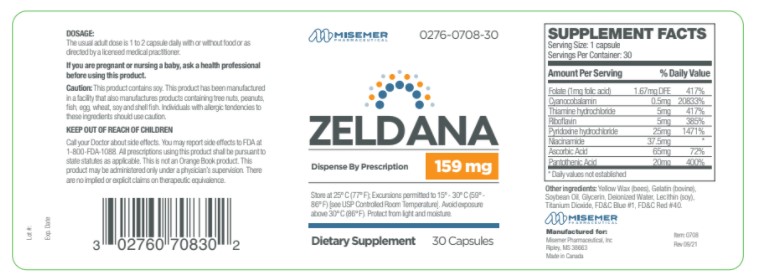 DRUG LABEL: Zeldana
NDC: 0276-0708 | Form: CAPSULE
Manufacturer: Misemer Pharmaceutical
Category: other | Type: Dietary Supplement
Date: 20211214

ACTIVE INGREDIENTS: FOLIC ACID 1 mg/1 1; CYANOCOBALAMIN .5 mg/1 1; THIAMINE HYDROCHLORIDE 5 mg/1 1; RIBOFLAVIN 5 mg/1 1; PYRIDOXINE HYDROCHLORIDE 25 mg/1 1; NIACINAMIDE 35.7 mg/1 1; ASCORBIC ACID 65 mg/1 1; PANTOTHENIC ACID 20 mg/1 1
INACTIVE INGREDIENTS: YELLOW WAX; GELATIN TYPE B BOVINE (150 BLOOM); SOYBEAN OIL; GLYCERIN; WATER; LECITHIN, SOYBEAN; TITANIUM DIOXIDE; FD&C BLUE NO. 1; FD&C RED NO. 40

Zeldana

HEALTH CLAIM

Zeldana is intended for the dietary management of a patient who, because of therapeutic or chronic medical needs, has limited or impaired chronic medical needs, has limited or impaired capacity to ingest, digest, absorb, or metabolize ordinary foodstuffs or certain nutrients, or who has other specific medically determined nutrient requirements, the dietary management of which cannot be achieved by the modification of a normal diet alone.

All prescriptions using this product shall be pursuant to state statutes as applicable. This is not an Orange Book product. This product may be administered only under physician's supervision. There are no implied or explicit claims on therapeutic equivilance

Manufactured for:

Misemer Pharmaceutical, Inc.

Ripley, MS 38663

Item 0708

Rev. 0821-1

DOSAGE AND ADMINISTRATION

Usual adult dosage is one to two capsule daily or as directed by a licensed medical practitioner. Zeldana capsules are supplied as purple capsules printed with "354", dispensed in HDPE plastic bottles of 30ct.

PRECAUTIONS

Folic Acid, when administered as a single agent in doses above .1mg daily, may obscure pernicious anemia in that hematologic remission can occur while neurological manifestations remain progressive. The .5 mg of cyanocobalamin contained in Zeldana has been shown to provide an adequate amount of cyanocobalamin to address this precaution. A safe upper limit of 100 mg per day has been established for the unsupervised medical use of pyridoxine. Consider all sources of pyridoxine supplementation when prescribing Zeldana.

If pregnant or planning to become pregnant or are currently breastfeeding, please contact your physician or health-care provider before using or continuing use.

ADVERSE REACTIONS

Allergic sensitization has been reported following both oral and parenteral administration of folic acid. Paresthesia and somnolence have been reported with pyridoxine HCl. Mild transient diarrhea, polycthemia vera, peripheral vascular thrombosis, itching transitory exanthema and feeling of swelling of entire body has been associated with cyanocobalamin.

DRUG INTERACTIONS

Pyridoxine supplements should not be given to patients receiving the drug levodopa, beause the action of levodopa is antagonized by pyidoxine. However, pyridoxine may be used concurrently in patients receiving a preparation containing both carbidopa and levodopa. Concurrent use of phenytoin and folacin (folic acid) may result in decreased phenytoin effectiveness.

PATIENT INFORMATION

Zeldana capsules are for use only under the direction and supervision of a licensed physician or health-care provider.

PREGNANCY and NURSING MOTHERS

Zeldana is not intended for use as a prenatal/postnatal multivitamin for lactating in non-lactating mothers. This product contains B Vitamins in active forms. Talk with your medical pratitioner before using if pregnant or lactating.

STATEMENT OF IDENTITY

Zeldana is an orally administered prescription supplement indicated for the distinct nutritional requirements of patients in need of dietary supplementation as determined by a licensed medical practitioner. Zeldana should be administered under the supervision of a licensed medical practitioner.

SAFE HANDLING WARNING

This product is contraindicated in patients with a known hypersensitivity to any of the ingredients. Folic acid alone is improper therapy in the treatment of pernicious anemia and other megaloblastic anemias where Vitamin B12 is deficient.

Store at controlled room temperature 15*-30*C (59*F-86*F). Keep in cool dry place. Call your doctor about side effects. You may report side effects to FDA at 1-800-FDA-1088. KEEP THIS OUT OF THE REACH OF CHILDREN.

Dispense by Prescription

WARNINGS

This product is contraindicated in patients with a known hypersensitivity to any of the ingredients. Zeldana should only be used under the diretion and supervision of a licensed medical practioner. Use with caution in patients that may have a medical condition, are pregnant, lactating, trying to conceive, under the age of 18, or taking medications.